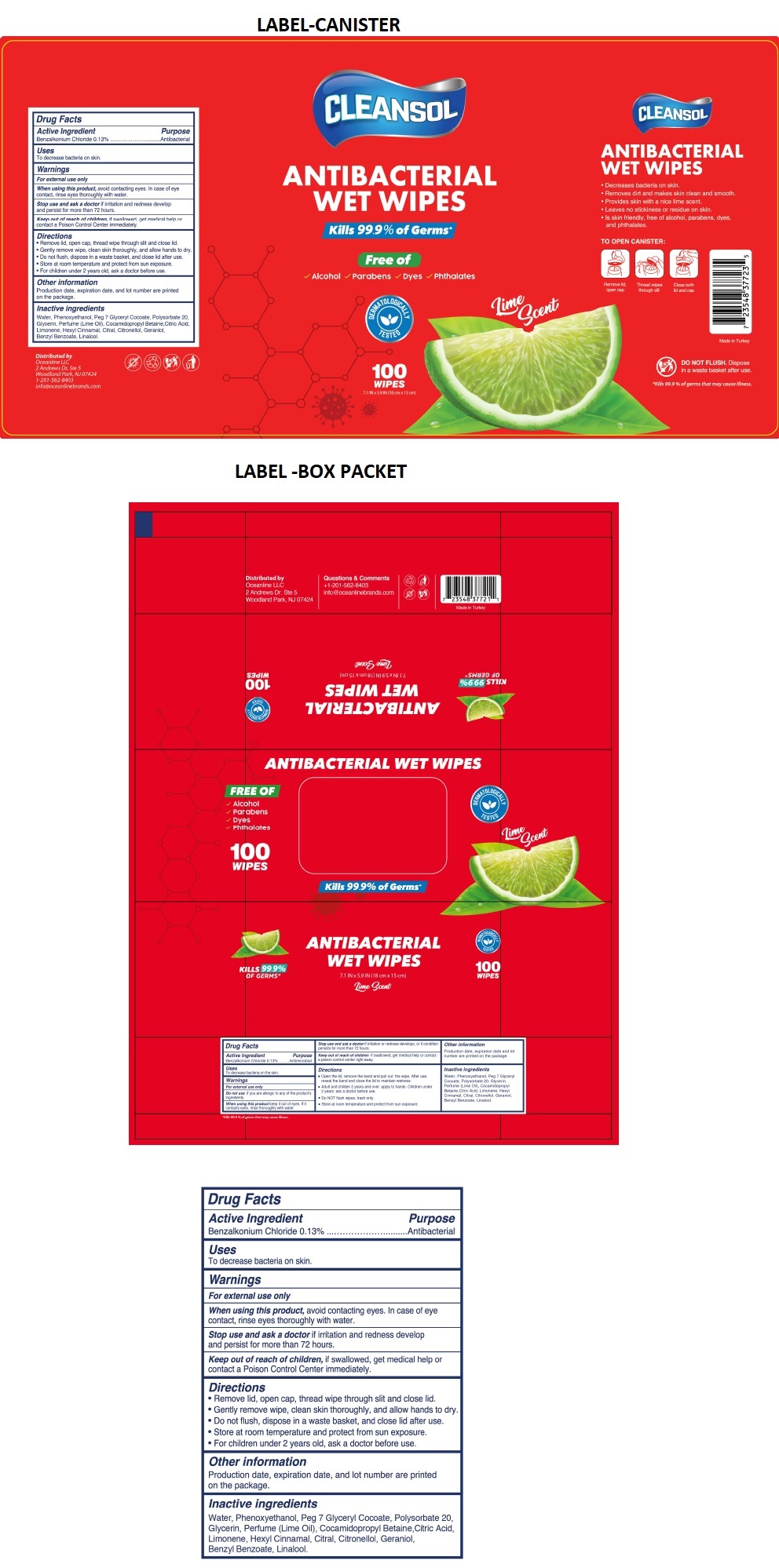 DRUG LABEL: CLEANSOL ANTIBACTERIAL WET WIPES
NDC: 78089-048 | Form: CLOTH
Manufacturer: Endeks Kimya Sanayi Ve Ticaret Anonim Sirketi
Category: otc | Type: HUMAN OTC DRUG LABEL
Date: 20200915

ACTIVE INGREDIENTS: BENZALKONIUM CHLORIDE 0.13 g/100 g
INACTIVE INGREDIENTS: WATER; PHENOXYETHANOL; PEG-7 GLYCERYL COCOATE; POLYSORBATE 20; GLYCERIN; LIME OIL; COCAMIDOPROPYL BETAINE; CITRIC ACID MONOHYDRATE; LIMONENE, (+)-; .ALPHA.-HEXYLCINNAMALDEHYDE; CITRAL; .BETA.-CITRONELLOL, (R)-; GERANIOL; BENZYL BENZOATE; LINALOOL, (+/-)-

CLEANSOL ANTIBACTERIAL WET WIPES Lime Scent

Active Ingredient

Benzalkonium Chloride 0.13%

Purpose

Antibacterial

Uses

To decrease bacteria on skin.

Warnings

For external use only

When using this product, avoid contacting eyes. In case of eye contact, rinse eyes thoroughly with water.

Stop use and ask a doctor if irritation and redness develop and persist for more than 72 hours.

Keep out of reach of children, if swallowed, get medical help or contact a Poison Control Center immediately.

Directions

• Remove lid, open cap, thread wipe through slit and close lid.

• Gently remove wipe, clean skin thoroughly, and allow hands to dry.

• Do not flush, dispose in a waste basket, and close lid after use.

• Store at room temperature and protect from sun exposure.

• For children under 2 years old, ask a doctor before use.

Other information

Production date, expiration date, and lot number are printed on the package.

Inactive ingredients

Water, Phenoxyethanol, Peg 7 Glyceryl Cocoate, Polysorbate 20, Glycerin, Perfume (Lime Oil), Cocamidopropyl Betaine, Citric Acid, Limonene, Hexyl Cinnamal, Citral, Citronellol, Geraniol, Benzyl Benzoate, Linalool.

Kills 99.9% of Germs*

Free of

Alcohol

Parabens

Dyes

Phthalates

DERMATOLOGICALLY TESTED

Distributed by

Oceanline LLC

2 Andrews Dr, Ste 5

Woodland Park, NJ 07424

Questions & Comments

+1-201-562-8403

info@oceanlinebrands.com

• Decreases bacteria on skin.

• Removes dirt and makes skin clean and smooth.

• Provides skin with a nice lime scent.

• Leaves no stickiness or residue on skin.

• Is skin friendly, free of alcohol, parabens, dyes, and phthalates.

TO OPEN CANISTER:

Remove lid, open cap

Thread wipes through slit

Close both lid and cap

Made in Turkey

DO NOT FLUSH. Dispose in a waste basket after use.

*Kills 99.9% of germs that may cause illness.